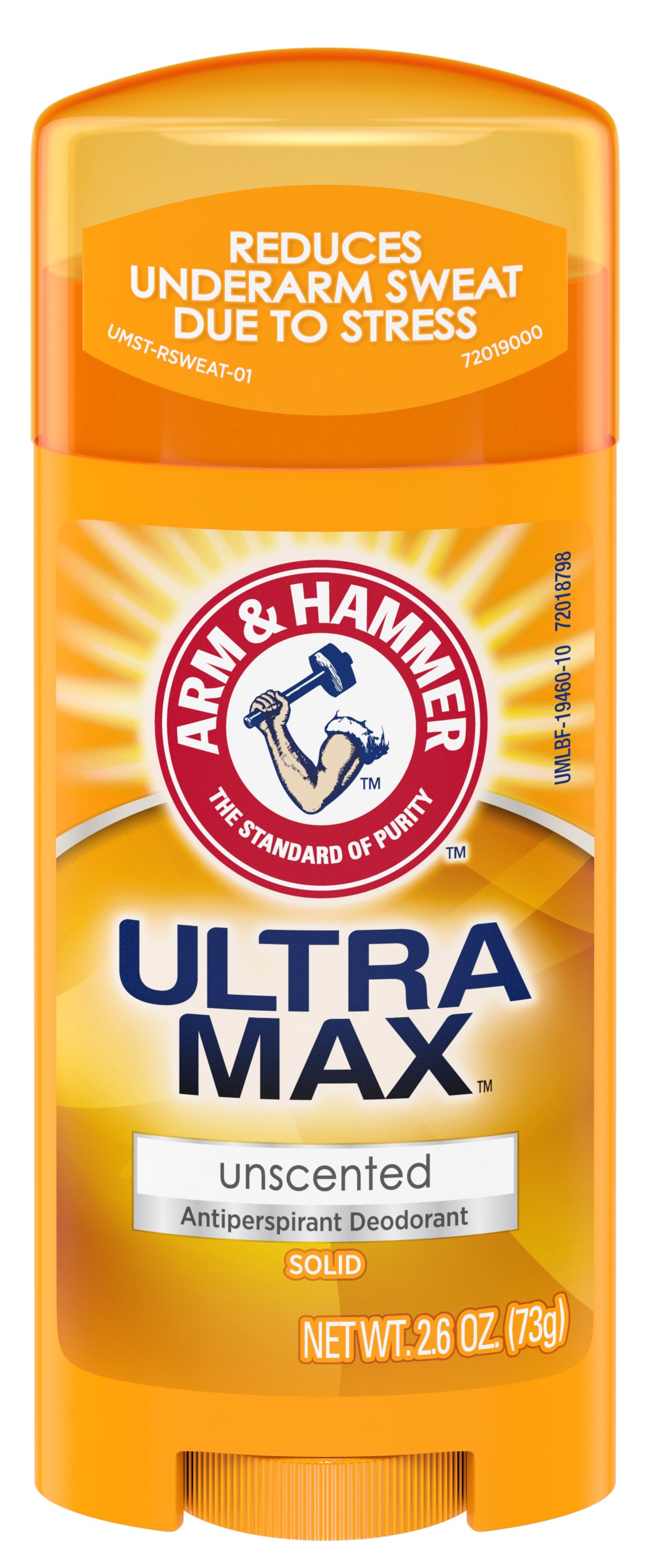 DRUG LABEL: UltraMax Invisible Solid - Unscented
NDC: 10237-873 | Form: STICK
Manufacturer: Church & Dwight Co., Inc.
Category: otc | Type: HUMAN OTC DRUG LABEL
Date: 20241120

ACTIVE INGREDIENTS: ALUMINUM CHLOROHYDRATE 0.19 g/1 g
INACTIVE INGREDIENTS: ETHYLENE BRASSYLATE; C12-20 ALKYL BENZOATE; PETROLATUM; CYCLOMETHICONE 5; STEARYL ALCOHOL; PPG-14 BUTYL ETHER; TALC; HYDROGENATED CASTOR OIL; SODIUM BICARBONATE; STARCH, CORN; XANTHAN GUM; MALTODEXTRIN

Arm and Hammer UltraMax Invisible Solid - Unscented

ACTIVE INGREDIENT

Aluminum Chlorohydrate 19%

PURPOSE

Antiperspirant

INDICATIONS AND USAGE

Usereduces underarm perspiration

WARNINGS

For external use only

Do not useon broken skin

Stop use ifrash or irritation occurs

Ask a doctor before use if you havekidney disease

Keep out of reach of children. If swallowed, get medical help or contact a Poison Control Center right away.

Directions

Apply a thin layer to underarms only

INACTIVE INGREDIENT

PPG-14 Butyl Ether, Cyclopentasiloxane, Stearyl Alcohol, C12-15 Alkyl Benzoate, Talc, Hydrogenated Castor Oil, Petrolatum, Ethylene Brassylate, Sodium Bicarbonate (Baking Soda), Corn Starch Modified, Polysaccharides, Maltodextrin

Questions or Comments?

Call 1-800-248-8820

M-F 9am-5pm ET

or visit www.ahultramax.com

PACKAGE LABEL

REDUCES

UNDERARM SWEAT

DUE TO STRESS

ARM AND HAMMER

THE STANDARD OF PURITY

ULTRA MAX

unscented

Antiperspirant Deodorant

SOLID

NET WT. 2.6 OZ. (73g)